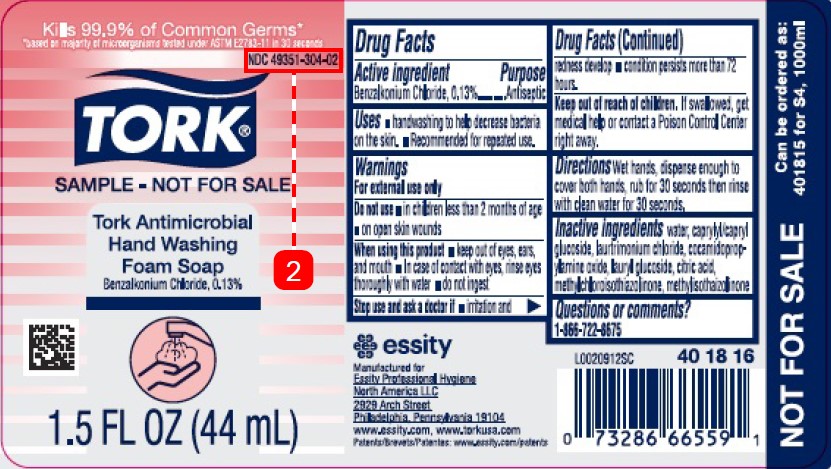 DRUG LABEL: Tork Hand Washing Antibacterial Foam
NDC: 49351-304 | Form: SOAP
Manufacturer: Essity Professional Hygiene North America LLC
Category: otc | Type: HUMAN OTC DRUG LABEL
Date: 20260204

ACTIVE INGREDIENTS: BENZALKONIUM CHLORIDE 1.3 mg/1 mL
INACTIVE INGREDIENTS: WATER; CAPRYLYL GLUCOSIDE; LAURTRIMONIUM CHLORIDE; COCAMIDOPROPYLAMINE OXIDE; LAURYL GLUCOSIDE; CITRIC ACID MONOHYDRATE; METHYLCHLOROISOTHIAZOLINONE; METHYLISOTHIAZOLINONE

Tork_Essity D17.002/D17AB
Antibacterial Foam Soap

Active ingredient

Benzalkonium Chloride 0.13%

Purpose

Antiseptic

Uses

- handwashing to help decrease bacteria on the skin
- recommended for repeated use

Warnings

For external use only

Do not use

- in children less than 2 months of age
- on open skin wounds

When using this product

- keep out of eyes, ears, and mouth. In case of contact with eyes, rinse eyes thoroughly with water.
- do not ingest

Stop use and ask a doctor if

- irritation and redness develop
- condition persists for more then 72 hours

Keep out of reach of children.

If swallowed, get medical help or contact a Poison Control Center right away.

Directions

- wet hands, dispense enough to cover both hands, rub for 30 seconds then rinse with clean water for 30 seconds

Inactive ingredients

water, caprylyl/capryl glucoside, laurtrimonium chloride, cocamidopropylamine oxide, lauryl glucoside, citric acid, methylcholorisothiazonlinone, methylisothiazolinone

Questions or comments?

1-866-722-8675

Disclaimer

NOT FOR SALE

Can be ordered as:

401815 for S4, 1000ml

Adverse reaction

essity

Manufactured for

Essity Professional Hygiene North America LLC

2929 Arch Street

Philadelphia, Pennsylvania 19104

www.essity.com, www.torkusa.com

Patents: www.essity.com/patents

Principal Panel Display

Kills 99.9% of Common Germs*

*based on majority of microorganisms tested under ASTM E2783-11 in 30 seconds

NDC 49351-304-02

TORK®

SAMPLE - NOT FOR SALE

Tork Antimicrobial Hand Washing Foam Soap

Benzalkonium Chloride 0.13%

1.5 FL OZ (44 mL)